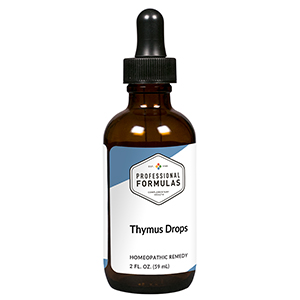 DRUG LABEL: Thymus Drops
NDC: 63083-5027 | Form: LIQUID
Manufacturer: Professional Complementary Health Formulas
Category: homeopathic | Type: HUMAN OTC DRUG LABEL
Date: 20190815

ACTIVE INGREDIENTS: ECHINACEA PURPUREA WHOLE 1 [hp_X]/59 mL; VIROLA SEBIFERA RESIN 3 [hp_X]/59 mL; CALCIUM SULFATE ANHYDROUS 4 [hp_X]/59 mL; ARSENIC TRIOXIDE 6 [hp_X]/59 mL; AMARYLLIS BELLADONNA WHOLE 6 [hp_X]/59 mL; BOS TAURUS BONE MARROW 6 [hp_X]/59 mL; CALCIUM FLUORIDE 6 [hp_X]/59 mL; SILICON DIOXIDE 6 [hp_X]/59 mL; BOS TAURUS SPLEEN 6 [hp_X]/59 mL; SULFUR IODIDE 6 [hp_X]/59 mL; HYSSOPUS OFFICINALIS WHOLE 6 [hp_X]/59 mL; CALCIUM SULFIDE 8 [hp_X]/59 mL; LACHESIS MUTA VENOM 12 [hp_X]/59 mL
INACTIVE INGREDIENTS: ALCOHOL; WATER

HTMD

ACTIVE INGREDIENTS

Echinacea purpurea 1X
Myristica sebifera 3X
Calcarea sulphurica 4X
Arsenicum album 6X
Belladonna 6X
Bone marrow 6X
Calcarea fluorica 6X
Silicea 6X
Spleen 6X
Sulphur iodatum 6X
Thymus 6X
Hepar sulphuris calcareum 8X
Lachesis mutus 12X

QUESTIONS

Professional Formulas

PO Box 2034 Lake Oswego, OR 97035

INDICATIONS

For the temporary relief of cough, shortness of breath, mild chest pain, or muscle weakness.*

PURPOSE

*Claims based on traditional homeopathic practice, not accepted medical evidence. Not FDA evaluated.

WARNINGS

Consult a doctor if condition worsens or if symptoms persist. Keep out of the reach of children. In case of overdose, get medical help or contact a poison control center right away. If pregnant or breastfeeding, ask a healthcare professional before use.

Keep out of the reach of children.

PREGNANCY OR BREAST FEEDING

If pregnant or breastfeeding, ask a healthcare professional before use.

DIRECTIONS

Place drops under tongue 30 minutes before/after meals. Adults and children 12 years and over: Take 10 drops up to 3 times per day. Consult a physician for use in children under 12 years of age.

OTHER INFORMATION

Tamper resistant. If seal is broken, do not use. After opening, close container tightly and store at room temperature away from heat.

INACTIVE INGREDIENTS

20% ethanol, purified water.

LABEL

Est 1985

Professional Formulas

Complementary Health

Thymus Drops

Homeopathic Remedy

2 FL. OZ. (59 mL)